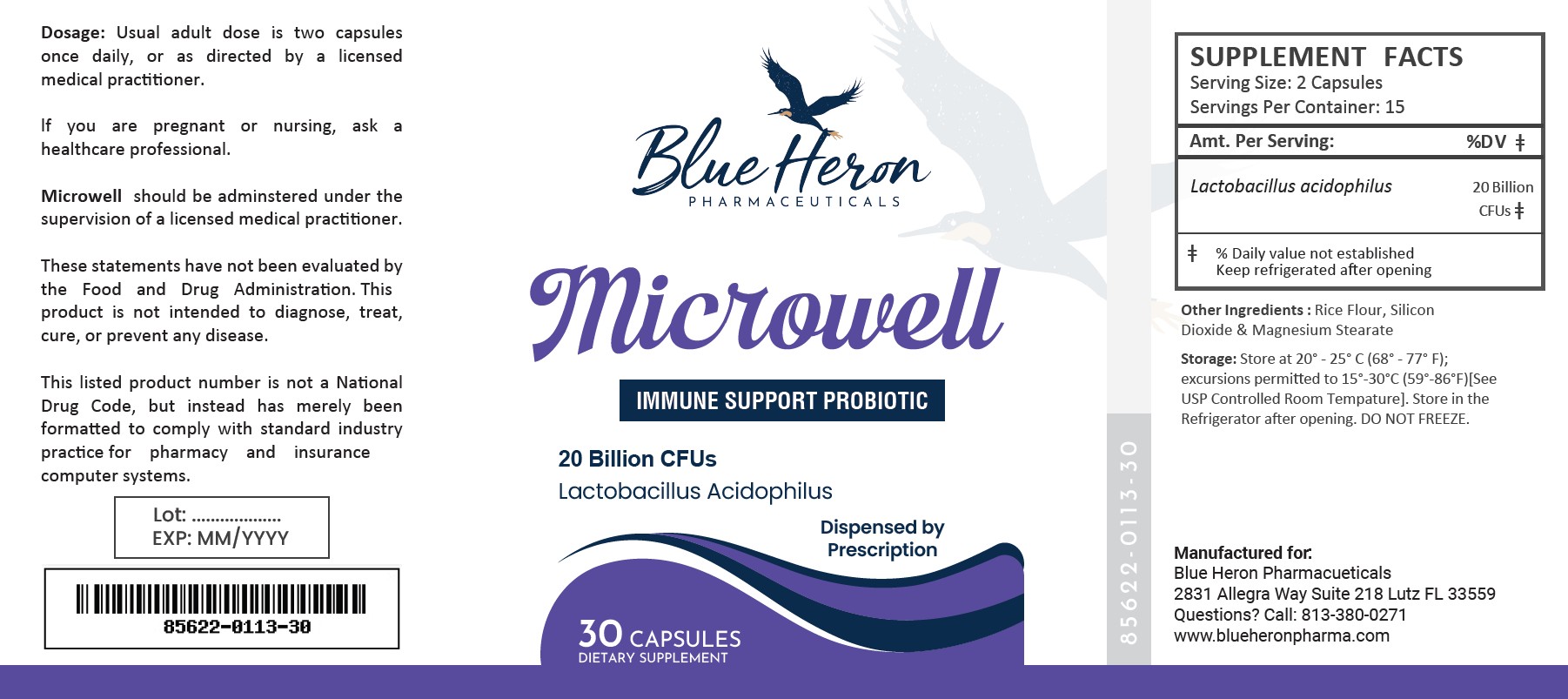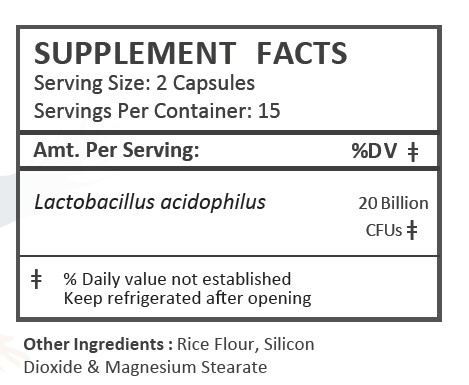 DRUG LABEL: Microwell
NDC: 85622-113 | Form: CAPSULE
Manufacturer: Blue Heron Pharmaceuticals, LLC
Category: other | Type: DIETARY SUPPLEMENT
Date: 20260212

ACTIVE INGREDIENTS: LACTOBACILLUS ACIDOPHILUS 20000000000 [CFU]/1 1

Microwell

HEALTH CLAIM:

Microwell Probiotic Capsules

Dispensed by Prescription

DESCRIPTION:

Microwell is an orally adminstered prescription probiotic dietary supplement.

Microwell Probiotic Capsules are clear capsules dispensed in plastic bottles of 30 ct.

85622-0113-30

Reserved for Professional Recommendation

This listed product is not a National Drug Code, but instead has merely been formatted to comply with standard industry practice for pharmacy and insurance computer systems.

These statements have not been evaluated by the Food and Drug Administration. This product is not intended to diagnose, treat, cure or prevent any disease.

All prescriptions using this product shall be pursuant to state statutes as applicable. This is not an Orange Book product. This product may be administered only under a physician’s supervision. There are no implied or explicit claims on therapeutic equivalence.

Manufactured for:

Blue Heron Pharmaceuticals

Lutz, FL 33559

WARNINGS AND PRECAUTIONS:

This product is contraindicated in patients with a known hypersensitivity to any of the ingredients.

As with any supplement, if you are pregnant, nursing, taking medication, or have a medical condition, ask a health professional before taking this product.

These statements have not been evaluated by the Food and Drug Administration. This product is not intended to diagnose, treat, cure, or prevent any disease.

DOSAGE AND ADMINISTRATION:

Usual adult dose is 2 capsules by mouth daily once daily, or as prescribed by a licensed medical practitioner.

Microwell is an orally administered prescription probiotic formulation for the clinical dietary management of suboptimal nutritional status in patients where advanced supplementation is required and nutritional supplementation in physiologically stressful conditions for maintenance of good health is needed.

PRECAUTIONS:

CONTRAINDICATIONS
This product is contraindicated in patients with known hypersensitivity to any of the ingredients.

PRECAUTIONS
This product is contraindicated in patients with a known hypersensitivity to any of the ingredients.

ADVERSE REACTIONS
Allergic sensitizations have been reported following oral administration of folic acid. Consult your physician immediately if adverse side effects occur.

KEEP OUT OF THE REACH OF CHILDREN.

STORAGE:

Handling (before opening):
Product is sensitive to moisture and heat. Keep bottle tightly closed in a dry, cool place. Store at 20^0C to 25^0C (68^0F to 77^0F).

Handling (after opening):
Store in the refrigerator after opening, DO NOT FREEZE. Store at 2^0C to 8^0C (35^0F to 46^0F).